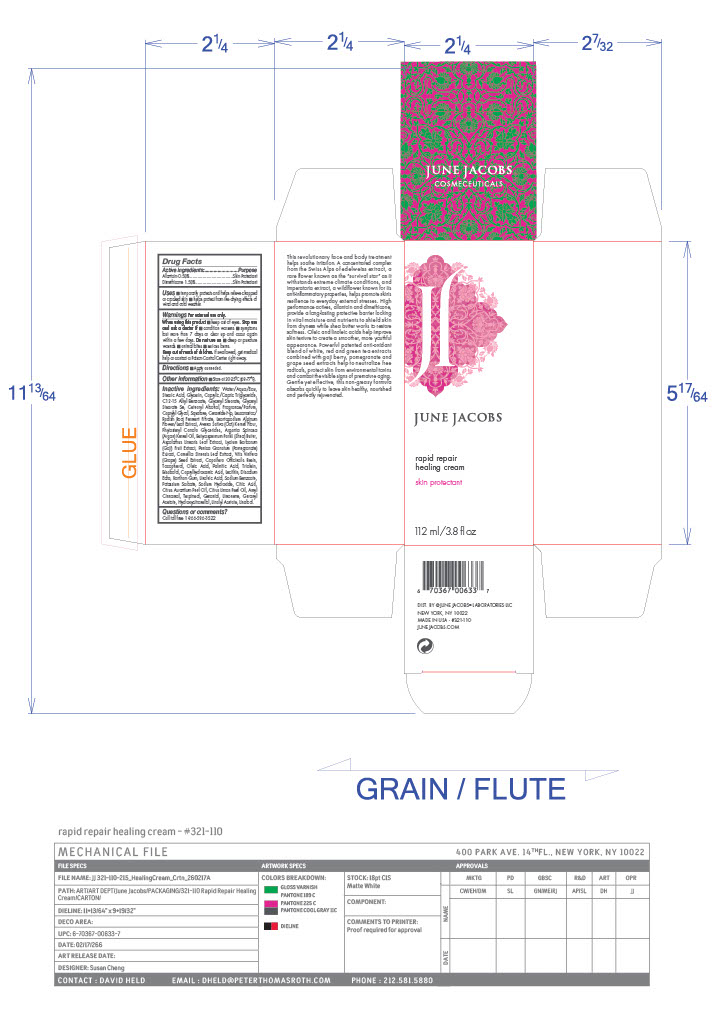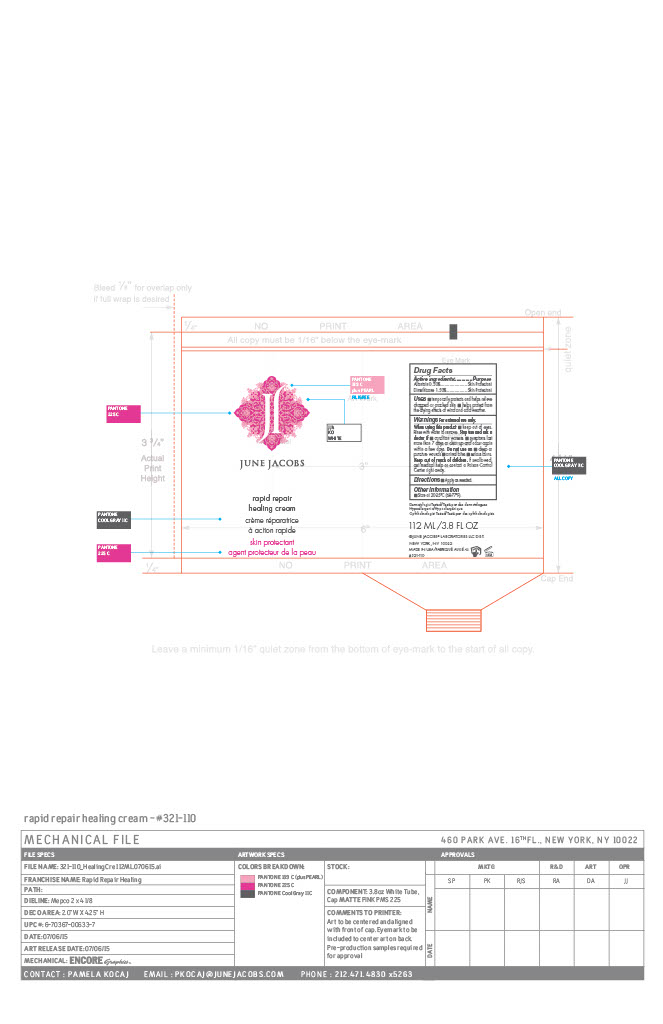 DRUG LABEL: Rapid Repair Healing Cream
NDC: 65278-110 | Form: CREAM
Manufacturer: June Jacobs Labs LLC
Category: otc | Type: HUMAN OTC DRUG LABEL
Date: 20260226

ACTIVE INGREDIENTS: ALLANTOIN 0.9907 g/198.14 g; DIMETHICONE 2.9721 g/198.14 g
INACTIVE INGREDIENTS: WATER; STEARIC ACID; CETEARYL ALCOHOL; COPAIFERA OFFICINALIS RESIN; OLEIC ACID; CAPRYLIC/CAPRIC TRIGLYCERIDE; XANTHAN GUM; GERANIOL; C12-15 ALKYL BENZOATE; GERANYL ACETATE; TRIOLEIN; CAPRYLHYDROXAMIC ACID; POTASSIUM SORBATE; ARGANIA SPINOSA KERNEL OIL; VITIS VINIFERA (GRAPE) SEED EXTRACT; PALMITIC ACID; EDETATE DISODIUM; GLYCERYL STEARATE; TOCOPHEROL; TERPINEOL; LINOLEIC ACID; GLYCERIN; OATMEAL; LECITHIN, SOYBEAN; CITRUS AURANTIUM PEEL OIL; CITRUS LIMON (LEMON) PEEL OIL; CITRIC ACID; AMYL CINNAMAL; SODIUM HYDROXIDE; LEUCONOSTOC/RADISH ROOT FERMENT FILTRATE; LYCIUM BARBARUM FRUIT; BISABOLOL; CAPRYLYL GLYCOL; SQUALANE; LIMONENE, (+)-; LINALYL ACETATE; CERAMIDE NP; SODIUM BENZOATE; BENZYL ACETATE; LEONTOPODIUM NIVALE SUBSP. ALPINUM FLOWERING TOP; PHYTOSTERYL MACADAMIATE; BUTYROSPERMUM PARKII (SHEA) BUTTER; ASPALATHUS LINEARIS LEAF; HYDROXYCITRONELLAL; LINALOOL; GLYCERYL STEARATE SE; METHYL ANTHRANILATE; PUNICA GRANATUM ROOT BARK; CAMELLIA SINENSIS LEAF

June Jacobs Rapid Repair Healing Cream

Active Ingredients

Allantoin- 0.50%

Dimethicone- 1.50%

Active Ingredient ...............................Purpose

Allantoin 0.50%...................................Skin protectant

Dimethicone 1.50%............................Skin protectant

Uses

- temporarily protects and helps relieve chapped or cracked skin.
- Helps protect from the drying effects of wind and cold weather.

Warnings For external use only.

When Using this product

- Keep out of the eyes. Rinse with water to remove.

Stop use and ask a doctor if

- Condition worsens
- Symptoms last more than 7 days or clear up and occur again within a few days.

Do not use on

- deep or puncture wounds
- animal bites
- serious burns

Keep out of reach of children.

if swallowed, get medical help or contact a Poison Control Center right away.

Directions

- Apply as needed

Other information:

- Store at 20-25C (68-77F)

Inactive Ingredients

Water/Aqua/Eau,
Stearic Acid, Glycerin, Caprylic/Capric Triglyceride, C12-15 Alkyl Benzoate, Glyceryl Stearate, Glyceryl Stearate Se, Cetearyl Alcohol, Fragrance/Parfum, Caprylyl Glycol, Squalane, Ceramide Np, Leuconostoc/Radish Root Ferment Filtrate, Leontopodium Alpinum Flower/Leaf Extract, Avena Sativa (Oat) Kernel Flour,Phytosteryl Canola Glycerides, Argania Spinosa (Argan) Kernel Oil, Butyrospermum Parkii (Shea) Butter, Aspalathus Linearis Leaf Extract, Lycium Barbarum (Goji) Fruit Extract, Punica Granatum (Pomegranate) Extract, Camellia Sinensis Leaf Extract, Vitis Vinifera (Grape) Seed Extract, Copaifera Officinalis Resin,Tocopherol, Oleic Acid, Palmitic Acid, Triolein, Bisabolol, Caprylhydroxamic Acid, Lecithin, Disodium Edta, Xanthan Gum, Linoleic Acid, Sodium Benzoate, Potassium Sorbate, Sodium Hydroxide, Citric Acid, Citrus Aurantium Peel Oil, Citrus Limon Peel Oil, Amyl Cinnamal, Terpineol, Geraniol, Limonene, Geranyl Acetate, Hydroxycitronellal, Linalyl Acetate, Linalool.